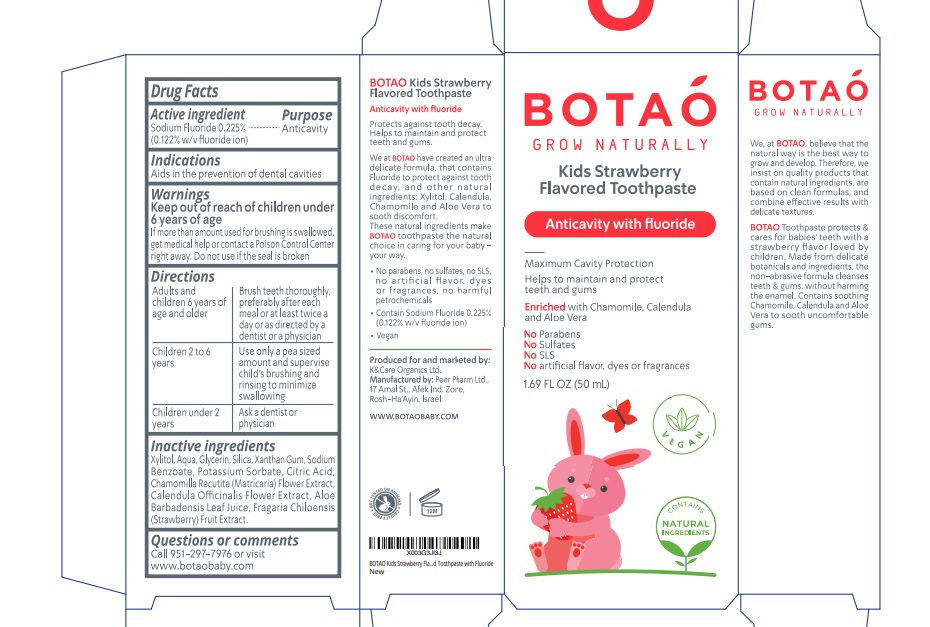 DRUG LABEL: Botao Kids Strawberry Flavored with Fluoride
NDC: 69435-1405 | Form: PASTE
Manufacturer: Peer Pharm Ltd.
Category: otc | Type: HUMAN OTC DRUG LABEL
Date: 20260112

ACTIVE INGREDIENTS: SODIUM FLUORIDE 0.122 g/100 mL
INACTIVE INGREDIENTS: XYLITOL; WATER; GLYCERIN; SILICON DIOXIDE; SODIUM BENZOATE; POTASSIUM SORBATE; XANTHAN GUM; STRAWBERRY; ANHYDROUS CITRIC ACID; CHAMOMILE; CALENDULA OFFICINALIS FLOWER; ALOE VERA LEAF

Botao Kids Strawberry Flavored Toothpaste with Fluoride

Active Ingredients

Sodium Fluoride 0.225%

(0.122% w/v fluoride ion)

Purpose

Anticavity

Uses

Helps to maintain and protect teeth and gums from the very first tooth

Warnings

Keep out of reach of children under 6 yeras of age.

If more than amount used for brushing is swallowed, get medical help or contact a Poison Control Center right away. Do not use if the seal is broken.

Directions

Adults and children 6 years of age and Older | Brush teeth thoroughly preferably after each meal or at least twice a day or as directed; by a dentist or a physician
Children 2 to 6 years | Use only a pea sized amount and supervise childs brushing and rinsing to minimize swallowing
Children under 2 years | Ask a dentist or physician

Directions

• Adults and children 6 years of age and Older : Brush teeth thoroughly, preferably after each meal or at least twice a day or as directed by a dentist or a physician
• Children 2 to 6 years : Use only a pea sized amount and supervise child’s brushing and rinsing to minimize swallowing
• Children under 2 years : Ask a dentist or physician

Directions

• Adults and children 6 years of age and Older : Brush teeth thoroughly, preferably after each meal or at least twice a day or as directed by a dentist or a physician
• Children 2 to 6 years : Use only a pea sized amount and supervise child’s brushing and rinsing to minimize swallowing
• Children under 2 years : Ask a dentist or physician

Inactive Ingredients

Aqua, Glyceryl Stearate SE, Cetyl Alcohol, Butyrospermum Parkii (Shea) Butter, Ricinus Communis (Castor) Seed Oil, Glycerin, Microcrystalline Cellulose, Caprylhydroxamic Acid, Xanthan Gum, Caprylyl Glycol, Bisabolol, Propanediol, Sodium Phytate, Chamomilla Recutita (Matricaria) Flower Extract, Calendula Officinalis Flower Extract, Aloe Barbadensis Leaf Juice

Questions or comments

Call 951-297-7976 or visit

www.botaobaby.com